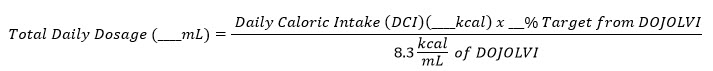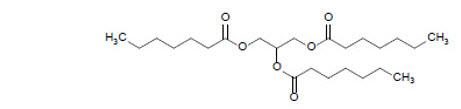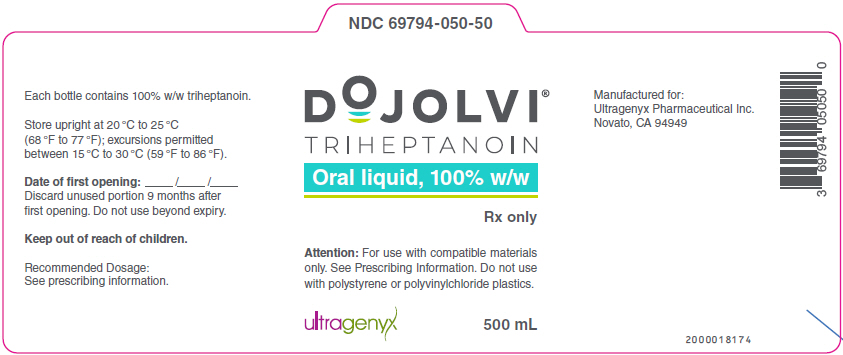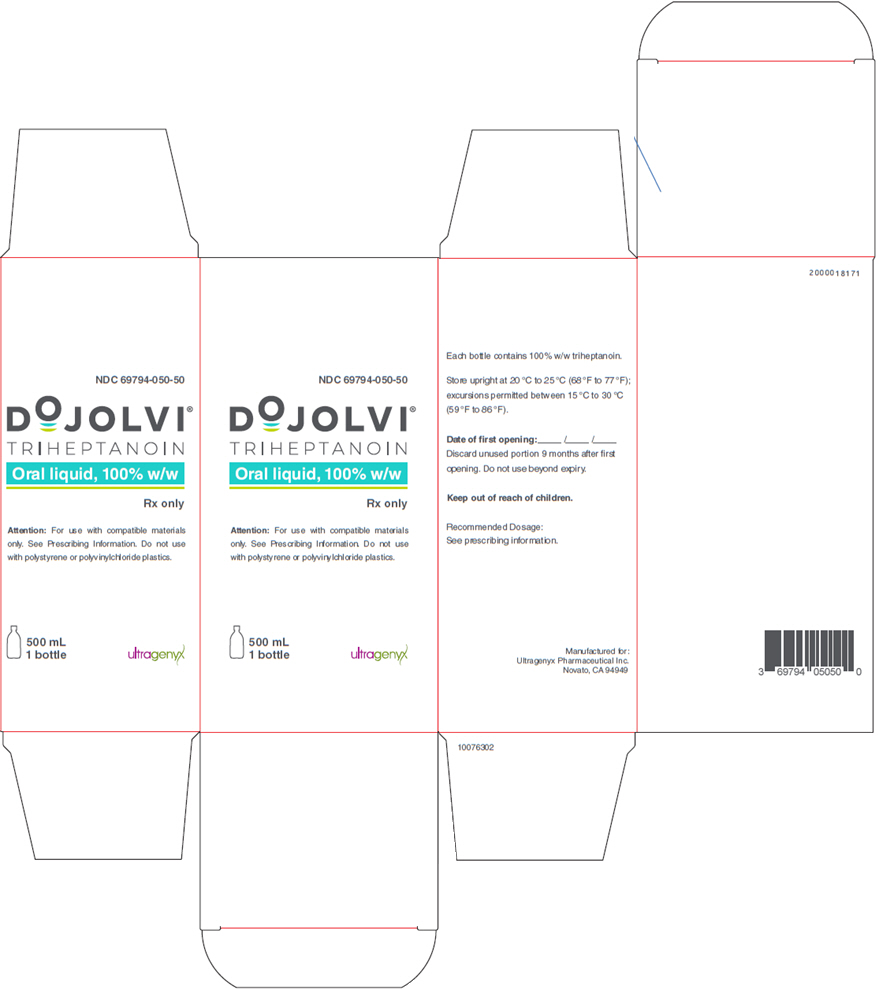 DRUG LABEL: DOJOLVI
NDC: 69794-050 | Form: LIQUID
Manufacturer: Ultragenyx Pharmaceutical Inc.
Category: prescription | Type: HUMAN PRESCRIPTION DRUG LABEL
Date: 20250610

ACTIVE INGREDIENTS: TRIHEPTANOIN 0.96 g/1 mL

HIGHLIGHTS OF PRESCRIBING INFORMATION

These highlights do not include all the information needed to use DOJOLVI safely and effectively. See full prescribing information for DOJOLVI.
DOJOLVI® (triheptanoin) oral liquid
Initial U.S. Approval: 2020

RECENT MAJOR CHANGES

Dosage and Administration (2.4) | 10/2023

1 INDICATIONS AND USAGE

DOJOLVI is a medium-chain triglyceride indicated as a source of calories and fatty acids for the treatment of adult and pediatric patients with molecularly confirmed long-chain fatty acid oxidation disorders (LC-FAOD).

2 DOSAGE AND ADMINISTRATION

- Assess metabolic requirements by determining daily caloric intake (DCI) prior to calculating the dose of DOJOLVI. (2.1)
- For patients receiving another medium-chain triglyceride product, discontinue prior to the first dose of DOJOLVI. (2.3)
- The recommended target daily dosage of DOJOLVI is up to 35% of the patient's total prescribed DCI divided into at least four doses and mixed thoroughly into semi-solid food/liquid or medical food/formula at mealtimes or with snacks. (2.2)
- See the full prescribing information for instructions on how to calculate the volume per dose; initiate and titrate the dosage to achieve the target; and prepare and administer DOJOLVI. (2.2, 2.3, 2.4)

3 DOSAGE FORMS AND STRENGTHS

Oral Liquid, 100% w/w of triheptanoin. (3)

4 CONTRAINDICATIONS

None.

5 WARNINGS AND PRECAUTIONS

- Feeding Tube Dysfunction: Regularly monitor the feeding tube to ensure proper functioning and integrity. (5.1)
- Intestinal Malabsorption in Patients with Pancreatic Insufficiency: Low or absent pancreatic enzymes may reduce absorption of DOJOLVI. Avoid administration of DOJOLVI in patients with pancreatic insufficiency. (5.2)

6 ADVERSE REACTIONS

Most common adverse reactions are (≥10%): abdominal pain, diarrhea, vomiting, and nausea. (6.1)

To report SUSPECTED ADVERSE REACTIONS, contact Ultragenyx Pharmaceutical Inc. at 1-888-756-8657 or FDA at 1-800-FDA-1088 or www.fda.gov/medwatch.

7 DRUG INTERACTIONS

- Pancreatic Lipase Inhibitors: Avoid co-administration due to potential for reduced clinical effect of DOJOLVI. (7.1)

FULL PRESCRIBING INFORMATION

1 INDICATIONS AND USAGE

DOJOLVI is indicated as a source of calories and fatty acids for the treatment of adult and pediatric patients with molecularly confirmed long-chain fatty acid oxidation disorders (LC-FAOD).

2 DOSAGE AND ADMINISTRATION

2.1 Important Recommendations Prior to DOJOLVI Treatment

All patients treated with DOJOLVI should be under the care of a clinical specialist knowledgeable in appropriate disease-related dietary management based upon current nutritional recommendations.

Assess the metabolic requirements of the patient by determining their daily caloric intake (DCI) prior to calculating the dose of DOJOLVI.

For patients receiving another medium-chain triglyceride (MCT) product, discontinue prior to the first dose of DOJOLVI.

2.2 Recommended Dosage

The recommended target daily dosage of DOJOLVI is up to 35% of the patient's total prescribed DCI divided into at least four doses and administered by mixing thoroughly into semi-solid food/liquid or medical food/formula at mealtimes or with snacks.

In order to reach a target daily dosage, patients may require an increase in their total fat intake.

The neonatal population may require higher fat intake and therefore an increased amount of DOJOLVI. Consider current nutritional recommendations when dosing the neonatal population.

Total Daily Dosage Calculation

The target daily dosage from DOJOLVI (%) is converted to a volume of DOJOLVI (mL) to be administered using the following calculation:

- Caloric value of DOJOLVI = 8.3 kcal/mL
- Round the total daily dosage to the nearest whole milliliter.
- Divide the total daily dosage into at least four approximately equal individual doses.

Missed Doses

If a dose is missed, take the next dose as soon as possible with subsequent doses taken at 3 to 4-hour intervals. Skip the missed dose if it will not be possible to take all doses in a day.

2.3 Dosage Initiation and Titration

For patients not currently taking an MCT product

Initiate DOJOLVI at a total daily dosage of approximately 10% DCI divided into at least four times per day. Increase to the recommended total daily dosage by approximately 5% DCI every 2 to 3 days until the target dosage of up to 35% DCI is achieved.

For patients switching from another MCT product

Discontinue use of MCT products before starting DOJOLVI.

Initiate DOJOLVI at the last tolerated daily dosage (mL) of MCT divided into at least four times per day. Increase the total daily dosage by approximately 5% DCI every 2 to 3 days until the target dosage of up to 35% DCI is achieved.

Tolerability

- Consider more frequent smaller doses if a patient has difficulty tolerating 1/4 of the total daily dosage at one time based on gastrointestinal adverse reactions [see Adverse Reactions (6.1)].
- Monitor the patient's total caloric intake during dosage titration, especially in a patient with gastrointestinal adverse reactions, and adjust all components of the diet as needed.
- If a patient experiences gastrointestinal adverse reaction(s), consider dosage reduction until the gastrointestinal symptoms resolve [see Adverse Reactions (6.1)].
- If a patient is unable to achieve the target daily dosage of up to 35% DCI during dosage titration, maintain the patient at the maximum tolerated dosage.

2.4 Preparation and Administration Instructions

Administer DOJOLVI by mixing thoroughly with semi-solid food/liquid (oral administration) or medical food/formula (feeding tube administration). Do not administer DOJOLVI alone to avoid gastrointestinal upset and feeding tube degradation [see Adverse Reactions (6.1)].

Prepare or administer DOJOLVI using containers, oral syringes, or measuring cups made of compatible materials such as stainless steel, glass, high density polyethylene (HDPE), polypropylene, low density polyethylene, polyurethane, and silicone.

Do not prepare or administer DOJOLVI using containers, oral syringes, or measuring cups made of polystyrene or polyvinyl chloride (PVC) plastics.

Regularly monitor the containers, dosing components, or utensils that are in contact with DOJOLVI to ensure proper functioning and integrity.

Oral Preparation and Administration

- Use an oral syringe or measuring cup made of compatible materials as listed above to withdraw the prescribed volume of DOJOLVI from the bottle.
- DOJOLVI can be mixed with soft food or liquid such as:
  - plain or artificially sweetened fat free yogurt
  - fat free milk, formula, or cottage cheese
  - whole grain hot cereal
  - fat free low carbohydrate pudding, smoothies, applesauce, or baby food
- Add the prescribed amount of DOJOLVI to a clean bowl, cup, or container, made of the compatible materials as listed above, which contains an appropriate amount of semi-solid food or liquid that takes into consideration the age, size, and fluid needs of the patient to ensure administration of the full dose.
- Mix DOJOLVI thoroughly into the food or liquid.
- Any unused mixture may be stored for up to 24 hours in refrigerated conditions.
- If not used within 24 hours, discard DOJOLVI mixture in the trash. Do not pour down the sink. Do not save for later.

Feeding Tube Preparation and Administration

DOJOLVI is administered as an oral or enteral bolus medication. Do not add DOJOLVI to the feeding bag, as the feeding equipment may degrade over time.

DOJOLVI can be administered via oral or enteral feeding tubes manufactured of silicone or polyurethane. Do not use feeding tubes manufactured of polyvinyl chloride (PVC). Feeding device performance and functionality can degrade over time depending on usage and environmental conditions. Regularly monitor the feeding tube to ensure proper functioning and integrity [see Warnings and Precautions (5.1)].

- Use an oral syringe or measuring cup made of compatible materials as listed above to withdraw the prescribed volume of DOJOLVI from the bottle.
- Add the prescribed amount of DOJOLVI to a clean bowl, cup, or container, made of compatible materials as listed above, which contains an amount of medical food or formula that takes into consideration the age, size, and fluid needs of the patient in order to ensure administration of the full dose.
- Mix DOJOLVI thoroughly into the medical food or formula prior to administering via feeding tube, y-connector, or feeding tube extension set made of silicone or polyurethane.
- Draw up the entire amount of the DOJOLVI mixture into a slip tip syringe.
- Remove the residual air from the syringe and connect the syringe directly into the feeding tube port.
- Push the syringe contents into the feeding tube port using steady pressure until empty.
- Flush the feeding tubes with between 5 mL to 30 mL of water. Flush volume should be modified based on specific patient needs and in cases of fluid restriction.
- Discard any unused DOJOLVI mixture in the trash. Do not pour down the sink. Do not save for later use.

3 DOSAGE FORMS AND STRENGTHS

Oral liquid: clear, colorless to light yellow liquid supplied in a 500 mL bottle containing 100% w/w of triheptanoin.

4 CONTRAINDICATIONS

None.

5 WARNINGS AND PRECAUTIONS

5.1 Feeding Tube Dysfunction

Feeding tube performance and functionality can degrade over time depending on usage and environmental conditions. In clinical trials, feeding tube dysfunction was reported in patients receiving triheptanoin. The contribution of DOJOLVI cannot be ruled out. Do not administer DOJOLVI in feeding tubes manufactured of polyvinyl chloride (PVC) [see Dosage and Administration (2.4]. Regularly monitor the feeding tube to ensure proper functioning and integrity.

5.2 Intestinal Malabsorption in Patients with Pancreatic Insufficiency

Pancreatic enzymes hydrolyze triheptanoin and release heptanoate as medium-chain fatty acids in the small intestine. Low or absent pancreatic enzymes may result in reduced absorption of heptanoate subsequently leading to insufficient supplementation of medium-chain fatty acids. Avoid administration of DOJOLVI in patients with pancreatic insufficiency.

6 ADVERSE REACTIONS

6.1 Clinical Trial Experience

Because clinical trials are conducted under widely varying conditions, adverse reaction rates observed in the clinical trials of a drug cannot be directly compared to rates in the clinical trials of another drug and may not reflect the rates observed in practice.

The safety population included 79 patients with LC-FAOD exposed to DOJOLVI in two studies: one open-label 78-week study of DOJOLVI in 29 patients (Study 1) followed by an open-label extension study (Study 2). Twenty-four patients from Study 1 continued into Study 2. Patients ranged from 4 months to 63 years of age and the population was 52% male. Of the 79 patients, 87% were White, 5% were Black or African-American, 4% were Asian, and 4% other. The daily dosage of DOJOLVI ranged between 12% and 41% DCI (which corresponds to 0.7 g/kg/day to 6.0 g/kg/day for pediatric patients and 0.5 g/kg/day to 1.3 g/kg/day for adult patients) for a mean duration of 23 months.

The most common adverse reactions to DOJOLVI reported in the pooled safety population of Study 1 and Study 2 were gastrointestinal (GI)-related, and included abdominal pain (abdominal discomfort, abdominal distension, abdominal pain, abdominal pain upper, GI pain) [60%], diarrhea [44%], vomiting [44%], and nausea [14%].

Gastrointestinal (GI) Adverse Reactions

In Study 1 and Study 2, median time to onset of a first occurrence of a GI adverse reaction was 7.3 weeks. GI adverse reactions led to dose reductions in 35% and 12% of patients in Study 1 and Study 2, respectively.

In Study 3, a 4-month double-blind randomized controlled study, commonly reported adverse reactions with triheptanoin were similar to those reported in Study 1 and Study 2.

7 DRUG INTERACTIONS

7.1 Pancreatic Lipase Inhibitors

Co-administration of triheptanoin with a pancreatic lipase inhibitor (e.g., orlistat) may reduce exposure to the triheptanoin metabolite, heptanoate, and reduce the clinical effect of triheptanoin [see Clinical Pharmacology (12.3)]. Avoid co-administration of DOJOLVI with pancreatic lipase inhibitors.

8 USE IN SPECIFIC POPULATIONS

8.1 Pregnancy

Risk Summary

There are no available data on triheptanoin use in pregnant women to evaluate for a drug-associated risk of major birth defects, miscarriage, or adverse maternal or fetal outcomes. In animal reproduction studies conducted in pregnant rats and rabbits administered triheptanoin during the period of organogenesis, the primary toxicological effect (reduced body weight gain) was considered to be specific to decreased food consumption related to taste aversion in animals, and therefore is not relevant to clinical use in the intended populations.

There is a pregnancy safety study for DOJOLVI. If a patient becomes pregnant while receiving DOJOLVI, healthcare providers should report DOJOLVI exposure by calling Ultragenyx Pharmaceutical Inc. at 1-888-756-8657.

The background risk of major birth defects and miscarriage for the indicated population is unknown. All pregnancies have a background risk of birth defect, loss or other adverse outcomes. In the U.S. general population, the estimated background risk of major birth defects and miscarriage in clinically recognized pregnancies is 2 to 4% and 15 to 20%, respectively.

Data

Animal Data

Embryofetal developmental studies have been conducted with triheptanoin in rats and rabbits following oral administration of 10% (3.2 g/kg), 30% (9.7 g/kg) and 50% (16 g/kg) DCI in rats and 10% (1.2 g/kg), 20% (2.3 g/kg) and 30% (3.5 g/kg) DCI in rabbits during the period of organogenesis. Reduced body weight gain, associated with decreased food consumption, was observed in pregnant rats and rabbits following administration of triheptanoin food mixture and was attributed to taste aversion. The NOAEL for this maternal toxicity (lack of body weight gain) was 10% DCI for both rats and rabbits. Administration of dietary triheptanoin to pregnant rats at doses approximately 2 times above, and pregnant rabbits approximately equal to the targeted clinical dose of 35% DCI resulted in increased incidence of skeletal malformations and decreased litter weights in both species and reduced number of viable litters in rabbits. The adverse effects on rat and rabbit embryofetal development were associated with the reduced body weight gain observed in pregnant animals. The NOAEL for embryofetal development toxicity was 30% and 20% DCI for rats and rabbits, respectively. In a pre- and postnatal developmental study in rats, reduced birthweights and delayed sexual maturation in pups were observed at 50% DCI and were considered secondary to the reductions in body weight gain in pregnant rats.

8.2 Lactation

Risk Summary

There are no data on the presence of triheptanoin or its metabolites in human or animal milk, the effects on the breastfed infant, or the effects on milk production. Medium-chain triglycerides and other fatty acids are normal components of breastmilk and the composition of breastmilk varies within feedings, over stages of lactation, and between mothers and populations due to maternal factors including genetics, environment, and diet. The developmental and health benefits of breastfeeding should be considered along with the clinical need for DOJOLVI and any potential adverse effect on the breastfed infant from DOJOLVI or from the underlying maternal condition.

8.4 Pediatric Use

The safety and effectiveness of DOJOLVI have been established in pediatric patients [see Adverse Reactions (6.1), Clinical Studies (14)].

8.5 Geriatric Use

Clinical studies of DOJOLVI did not include patients 65 years of age and older to determine if they respond differently from younger adult patients.

11 DESCRIPTION

DOJOLVI (triheptanoin) is a synthetic medium odd-chain (C7) triglyceride supplied as a colorless to light yellow clear oral liquid. The chemical name of triheptanoin is heptanoic acid, 1,1',1''-(1,2,3-propanetriyl) ester. The empirical formula is C24H44O6 and its molecular weight is 428.6 g/mol. The chemical structure is:

The caloric value of triheptanoin is 8.3 kcal/mL. The fat content is 0.96 g/mL.

12 CLINICAL PHARMACOLOGY

12.1 Mechanism of Action

Triheptanoin is a medium-chain triglyceride consisting of three odd-chain 7-carbon length fatty acids (heptanoate) that provide a source of calories and fatty acids to bypass the long-chain FAOD enzyme deficiencies for energy production and replacement.

12.2 Pharmacodynamics

No formal pharmacodynamic studies have been conducted with DOJOLVI.

12.3 Pharmacokinetics

Following oral administration, triheptanoin is extensively hydrolyzed to heptanoate and glycerol by pancreatic lipases in the intestines. The exposure of triheptanoin in the human plasma is minimal. Pharmacokinetics of heptanoate exhibits high inter-patient variability. Heptanoate exposure increases greater than dose-proportional in the dose range between triheptanoin 0.3 and 0.4 g/kg.

Absorption

The pharmacokinetics of heptanoate in healthy adult subjects following an oral administration of DOJOLVI mixed with food are summarized in Table 1.

Table 1: Summary of Pharmacokinetic Parameters of Heptanoate after Single and Multiple Oral Administration of DOJOLVI to Healthy Adults (N = 13)
 | DOJOLVI Dose | Mean (SD) Cmax (µmol/L) | Mean (SD) AUC0-8h (µmol*hr/L) | Time to First Peak Concentration [After oral administration of DOJOLVI, more than one peak concentration of heptanoate is observed.] Median (range) (hours)
Single Dose | 0.3 g/kg | 178.9 (145) | 336.5 (223) | 0.5 (0.4 to 1.0)
Single Dose | 0.4 g/kg | 259.1 (134) | 569.1 (189) | 0.8 (0.4 to 6.4)
Multiple Doses | 0.3 g/kg administered 4 times a day for 2 days (total daily dosage of 1.3 g/kg/day) | 319.9 (164) | 789.8 (346) | 1.2 (0.0 to 2.4)
Multiple Doses

Distribution

The plasma protein binding of heptanoate is approximately 80% and is independent of total concentration.

Elimination

After a single dose of either 0.3 g/kg or 0.4 g/kg triheptanoin to healthy subjects, the mean apparent clearance (CL/F) of heptanoate was 6.05 and 4.31 L/hr/kg, respectively. Half-life (t1/2) of heptanoate could not be determined due to multiple peak concentrations of heptanoate observed.

Metabolism

Heptanoate, formed by hydrolysis of triheptanoin, can be metabolized to beta-hydroxypentanoate (BHP) and beta-hydroxybutyrate (BHB) in the liver.

Excretion

After single or multiple repeat doses of triheptanoin to healthy subjects, triheptanoin and its metabolites were minimally excreted in urine.

Drug Interaction Studies

In Vitro Studies

Heptanoate is not an inhibitor of CYP1A2, CYP2B6, CYP2C8, CYP2C9, CYP2C19, CYP2D6, or CYP3A4. Heptanoate and BHP are not CYP substrates nor UGT substrates. Heptanoate increases the unbound fraction of valproic acid by approximately 2-fold.

13 NONCLINICAL TOXICOLOGY

13.1 Carcinogenesis, Mutagenesis, Impairment of Fertility

Carcinogenesis

Nonclinical animal studies evaluating long-term administration of triheptanoin have not been conducted to assess the carcinogenic potential of the drug. In a published chronic 9-month dietary study conducted in rats, daily administration of triheptanoin at dose levels up to 1.14 g/kg was associated with atrophy or hyperplasia of the intestinal villa. In a chronic 9-month dietary study conducted in juvenile minipigs, treatment with triheptanoin at dose levels up to 10 g/kg was well tolerated with no changes in histopathology suggestive of any carcinogenic potential.

Published studies with structurally similar triglycerides (i.e., MCTs) were also evaluated. In a 2-year dietary study of rats fed tricaprylin (C8 MCT) at dose levels up to 9.5 g/kg (approximately 1.2 times the anticipated maximum clinical dose), there were increased incidences of pancreatic and forestomach hyperplasia and adenomas but not carcinomas. Chronic administration of a diet containing approximately 17% MCT was not shown to promote effects on colon tumor incidence in an azomethane-induced colon tumorigenicity rat model.

Mutagenesis

Triheptanoin was not genotoxic in a battery of genotoxicity tests including the in vitro bacterial reverse mutation in S. typhimurium and E. coli, in vitro mammalian chromosomal aberration test in human peripheral blood lymphocytes and the in vivo mammalian erythrocyte micronucleus test in rat bone marrow.

Impairment of Fertility

Triheptanoin had no effect on fertility or any other parameters of mating performance in rats exposed to repeat dietary administration at dose levels equivalent to up to 50% daily caloric intake (16 g/kg) that resulted in systemic drug exposure (AUC) of heptanoate approximately equal to the maximum recommended human dose.

14 CLINICAL STUDIES

The efficacy of triheptanoin as a source of calories and fatty acids was evaluated in Study 3 (NCT01379625), a 4-month double-blind randomized controlled study comparing triheptanoin (7-carbon chain fatty acid) with trioctanoin (8-carbon chain fatty acid). The study enrolled 32 adult and pediatric patients with a confirmed diagnosis of LC-FAOD and evidence of at least one significant episode of rhabdomyolysis and at least two of the following diagnostic criteria: disease specific elevation of acylcarnitines on a newborn blood spot or in plasma, low enzyme activity in cultured fibroblasts, or one or more known pathogenic mutations in CPT2, ACADVL, HADHA, or HADHB.

The dosage of study drug was titrated to a protocol-specified target of 20% DCI (actual mean daily dose achieved was 16% for triheptanoin and 14% for trioctanoin). The recommended target dosage of DOJOLVI is up to 35% of DCI [see Dosage and Administration (2.2)]. Patients ranged in age from 7 years to 64 years (median 24 years) and 12 were male. Of the 32 patients, 100% were White and 3% were Hispanic.

Baseline cardiovascular function in both groups was normal and within test/retest variability normally observed in repeated echocardiograms. After 4 months, patients in both groups had similar mean changes from baseline in left ventricular ejection fraction and wall mass on resting echocardiogram and similar maximal heart rates on treadmill ergometry.

Five patients experienced 7 events of rhabdomyolysis in the triheptanoin group and 4 patients experienced 7 events of rhabdomyolysis in the trioctanoin group.

No differences were observed between triheptanoin and trioctanoin groups in blood markers of metabolism including glucose, insulin, lactate, total serum, ketones, acylcarnitines, and serum-free fatty acid concentrations.

16 HOW SUPPLIED/STORAGE AND HANDLING

DOJOLVI (triheptanoin) oral liquid is supplied in a glass bottle as follows:

500 mL bottle | NDC 69794-050-50

STORAGE AND HANDLING

Store at 20° to 25°C (68° to 77°F); excursions permitted to 15° to 30°C (59° to 86°F) (see USP Controlled Room Temperature). Do not freeze.

DOJOLVI can be used for up to 9 months after opening but not beyond the expiration date on the bottle.

Do not dose or store using materials made of polystyrene or polyvinyl chloride (PVC) containers [see Dosage and Administration (2.4)].

Pharmacist: Dispense only in glass or HDPE bottles.

17 PATIENT COUNSELING INFORMATION

Advise the patient and/or caregiver to read the FDA-approved patient labeling (Patient Information and Instructions for Use).

Preparation and Administration

Instruct the patient or caregiver:

- To read the Instructions for Use for appropriate preparation and administration instructions on oral versus feeding tube administration.
- Before administration, to mix DOJOLVI thoroughly into semi-solid food/liquid (oral) or medical food/formula (feeding tube) at mealtimes or with snacks.
- To not prepare or administer DOJOLVI using containers, oral syringes, or measuring cups made of polystyrene or polyvinyl chloride (PVC) plastics.
- That if a dose is missed, to take the next dose as soon as possible with subsequent doses taken at 3 to 4-hour intervals. Skip the missed dose if it will not be possible to take all doses in a day [see Dosage and Administration (2.2)].

Storage

Instruct the patient or caregiver to store DOJOLVI at room temperature in the bottle in which it was dispensed [see How Supplied/Storage and Handling (16)].

Feeding Tube Dysfunction

Advise the patient or caregiver to regularly monitor the feeding tube for proper functioning and integrity and report to the healthcare provider if any issues are identified [see Warnings and Precautions (5.1)].

Intestinal Malabsorption in Patients with Pancreatic Insufficiency

Inform the patient or caregiver that pancreatic insufficiency may reduce the clinical effect of DOJOLVI. Any known pancreatic insufficiency should be reported to the healthcare provider [see Warnings and Precautions (5.2)].

Pregnancy

Advise a patient who is exposed to DOJOLVI during pregnancy that there is a pregnancy safety study that monitors pregnancy outcomes. Encourage the patient to report the pregnancy to Ultragenyx Pharmaceutical Inc. at 1-888-756-8657 [see Use in Specific Populations (8.1)].

Manufactured for:
Ultragenyx Pharmaceutical Inc.
60 Leveroni Court
Novato, CA 94949

PATIENT INFORMATION
DOJOLVI (doh-johl-vee)
(triheptanoin)
oral liquid

What is DOJOLVI?
DOJOLVI is a prescription medicine used to treat long-chain fatty acid oxidation disorders (LC-FAOD) in children and adults.

Before taking DOJOLVI, tell your healthcare provider about all of your medical conditions, including if you:

- are pregnant or plan to become pregnant. It is not known if DOJOLVI will harm your unborn baby.
  Pregnancy Safety Study. There is a pregnancy safety study for women who take DOJOLVI during pregnancy. The purpose of this study is to collect information about your health and your baby's health. You can talk to your healthcare provider or contact 1-888-756-8657 to enroll in this study or get more information.
- are breastfeeding or plan to breastfeed. It is not known if DOJOLVI passes into breast milk. Talk to your healthcare provider about the best way to feed your baby if you take DOJOLVI.
- are taking a pancreatic lipase inhibitor, such as orlistat, as it may affect how well DOJOLVI works.

Tell your healthcare provider about all the medicines you take, including prescription and over-the-counter medicines, vitamins, and herbal supplements.

How should I take DOJOLVI?

- See the detailed "Instructions for Use" at the end of this Patient Information Leaflet for instructions about how to mix and take DOJOLVI by mouth in soft food or drink or how to mix and give DOJOLVI in medical food or formula through feeding tubes.
- Take DOJOLVI exactly as your healthcare provider tells you.
- Your healthcare provider may start you on a low dose of DOJOLVI and slowly increase your dose to help avoid side effects. If you are taking another medium chain triglyceride (MCT) product, stop taking the MCT before starting DOJOLVI.
- Do not mix or give DOJOLVI using containers, oral syringes, or measuring cups made of polystyrene (a type of plastic that can be solid or foam) or polyvinyl chloride (PVC), a solid plastic material.
- Take DOJOLVI at least 4 times a day with meals or snacks, and always mix well with soft food or drink or medical food or formula before taking.

What are the possible side effects of DOJOLVI?

- Feeding tube problems. Feeding tubes may not work as well or stop working over time when taking DOJOLVI. Do not use DOJOLVI in feeding tubes made of polyvinyl chloride (PVC). Check the feeding tube to make sure it is working properly and not breaking down.
- Intestinal absorption problems in patients with pancreatic insufficiency. If you have pancreatic insufficiency, consult with your healthcare provider as it may affect how well DOJOLVI works.
- The most common side effects of DOJOLVI include:

- stomach (abdominal) pain
- diarrhea

- vomiting
- nausea

These are not all the possible side effects of DOJOLVI. Call your healthcare provider for medical advice about side effects. You may report side effects to Ultragenyx at 1-888-756-8657 or FDA at 1-800-FDA-1088.

How should I store DOJOLVI?

- Store DOJOLVI at room temperature between 68°F to 77°F.
- Do not freeze DOJOLVI.
- When the bottle of DOJOLVI has been opened, use within 9 months or by the expiration date on the bottle, whichever comes first.
- Do not store DOJOLVI in containers made of polystyrene or polyvinyl chloride (PVC).

General information about the safe and effective use of DOJOLVI.
Medicines are sometimes prescribed for purposes other than those listed in a Patient Information Leaflet. Do not use DOJOLVI for a condition for which it was not prescribed. Do not give DOJOLVI to other people, even if they have the same symptoms that you have. It may harm them. You can ask your pharmacist or healthcare provider for information about DOJOLVI that is written for health professionals.

What are the ingredients in DOJOLVI?
DOJOLVI is made of 100% triheptanoin and contains no other ingredients.
Manufactured for:
Ultragenyx Pharmaceutical Inc.
60 Leveroni Court
Novato, CA 94949
For more information, go to www.dojolvi.com or call 1-888-756-8657.

This Patient Information has been approved by the U.S. Food and Drug Administration.

Revised: 10/2023

INSTRUCTIONS FOR USE DOJOLVI (doh-johl-vee) (triheptanoin) oral liquid

This Instructions for Use contains information on how to take DOJOLVI. Read this Instructions for Use before you start taking DOJOLVI and each time you get a refill. There may be new information. This Instructions for Use does not take the place of talking to your healthcare provider about your medical condition or treatment.

Important Information You Need to Know Before Taking or Giving DOJOLVI:

- Use an oral syringe or measuring cup to measure your prescribed dose. Ask your healthcare provider or pharmacist to show you how to measure your prescribed dose.
- Mix or give DOJOLVI using containers, oral syringes, or measuring cups made of materials such as stainless steel, glass, or high density polyethylene (HDPE), polypropylene, low density polyethylene, polyurethane, and silicone (types of plastic materials).
- After use, rinse materials and containers well with cold water and wipe dry.
- Do not mix or give DOJOLVI using containers, oral syringes, or measuring cups made of polystyrene (a type of plastic that can be solid or foam) or polyvinyl chloride (PVC), a solid plastic material.
- Take DOJOLVI at least 4 times a day with meals or snacks, and always mix well with soft food or drink or medical food or formula before taking.
- If you take DOJOLVI by mouth, mix well with soft food or drink such as:
  - plain or artificially sweetened fat free yogurt
  - fat free milk, formula, or cottage cheese
  - whole grain hot cereal
  - fat free low carbohydrate pudding, smoothies, applesauce, or baby food
- If you give DOJOLVI by feeding tube, mix well with medical food or formula.
- Your healthcare provider should advise you on how to maintain a proper diet when taking DOJOLVI.
- If you miss a dose, take the next dose as soon as possible. Take the following doses 3 to 4 hours apart. If it is not possible to take all the doses for the day, skip the missed dose.

Taking DOJOLVI by mouth:

1. Use an oral syringe or measuring cup made of the materials listed above to measure the prescribed amount of DOJOLVI from the bottle.
2. Add the prescribed amount of DOJOLVI to a clean bowl, cup, or container, made of the materials listed above, containing the appropriate amount of soft food or drink as instructed by your healthcare provider.
3. Mix DOJOLVI well into the soft food or liquid and swallow the mixture.
4. Do not take DOJOLVI alone to avoid stomach upset.
5. You can store any unused DOJOLVI mixture for up to 24 hours in the refrigerator.
6. If not used within 24 hours, throw away (dispose of) the DOJOLVI mixture in the trash. Do not pour down the sink. Do not save for later.
7. Check the items used to take DOJOLVI often to make sure they are working properly and are not breaking down.

Giving DOJOLVI by feeding tube:

1. You can give DOJOLVI by a feeding tube.
2. Mix DOJOLVI with medical food or formula before giving by a feeding tube, y-connector, or feeding tube extension set.
3. Only give DOJOLVI in a feeding tube made of silicone or polyurethane.
4. Do not give DOJOLVI in a feeding tube made of polyvinyl chloride (PVC), a type of plastic.
5. Do not give DOJOLVI alone to avoid stomach upset and to avoid breakdown of the feeding tube.
6. Do not add DOJOLVI to the feeding bag because the feeding equipment may break down over time.
7. Use an oral syringe or measuring cup made of the materials listed above to measure the prescribed amount of DOJOLVI from the bottle.
8. Add the prescribed amount of DOJOLVI to a clean bowl, cup, or container, made of the materials listed above, containing the appropriate amount of medical food or formula as instructed by your healthcare provider.
9. Mix DOJOLVI well into the medical food or formula and draw up the entire amount of the mixture into a slip tip syringe.
10. Remove the air from the syringe and connect the syringe directly into the feeding tube port.
11. Push the contents of the syringe (DOJOLVI mixture) into the feeding tube port using steady pressure until empty.
12. Draw up about 5 mL to 30 mL of water with the slip tip syringe and flush the feeding tube feeding port with the water.
13. Throw away (dispose of) any unused DOJOLVI mixture in the trash. Do not pour down the sink. Do not save for later use.
14. Check the feeding tube and other items used to give DOJOLVI often to make sure they are working properly and are not breaking down.

How should I store DOJOLVI?

- Store DOJOLVI at room temperature between 68°F to 77°F (20°C to 25°C).
- Do not freeze DOJOLVI.
- When the bottle of DOJOLVI has been opened, use within 9 months or by the expiration date on the bottle, whichever comes first.
- Do not store DOJOLVI in containers made of polystyrene or polyvinyl chloride (PVC).

Keep DOJOLVI and all medicines out of the reach of children.
This Instructions for Use has been approved by the U.S. Food and Drug Administration.

Revised: 10/2023

PRINCIPAL DISPLAY PANEL - 500 mL Bottle Label

NDC 69794-050-50

DOJOLVI®
TRIHEPTANOIN
Oral liquid, 100% w/w
Rx only

Attention: For use with compatible materials
only. See Prescribing Information. Do not use
with polystyrene or polyvinylchloride plastics.

ultragenyx
500 mL

PRINCIPAL DISPLAY PANEL - 500 mL Bottle Carton

NDC 69794-050-50

DOJOLVI®
TRIHEPTANOIN
Oral liquid, 100% w/w
Rx only

Attention: For use with compatible materials
only. See Prescribing Information. Do not use
with polystyrene or polyvinylchloride plastics.

500 mL
1 bottle

ultragenyx